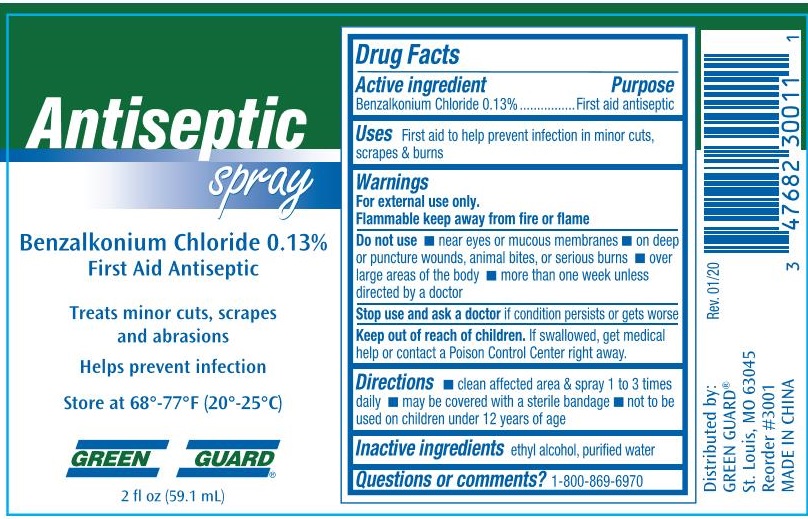 DRUG LABEL: Green Guard Antiseptic
NDC: 47682-333 | Form: SPRAY
Manufacturer: Unifirst First Aid Corporation
Category: otc | Type: HUMAN OTC DRUG LABEL
Date: 20250908

ACTIVE INGREDIENTS: BENZALKONIUM CHLORIDE 1.3 g/1 L
INACTIVE INGREDIENTS: ALCOHOL; WATER

Green Guard First Aid & Safety Antiseptic Spray

Active ingredient

Benzalkonium Chloride 0.13%

Purpose

First aid antiseptic

Uses

First aid to help prevent infection in minor cuts, scrapes and burns

Warnings

For external use only.

Flammable keep away from tire or flame

Do not use

- near eyes or mucous membranes
- on deep or puncture wounds, animal bites, or serious burns
- over large areas of the body
- more than one week unless directed by a doctor

Stop use and ask a doctor if condition persists or gets worse

Keep out of reach of children. If swallowed, get medical help or contact a Poison Control Center right away.

Directions

- clean affected area & spray 1 to 3 times daily
- may be covered with a sterile bandage
- not to be used on children under 12 years of age

Inactive ingredients

ethyl alcohol, purified water

Questions or comments? 1-800-869-6970

Green Gurad Antiseptic Spray Label

Antiseptic spray

Benzalkonium Chloride 0.13%

First Aid Antiseptic

Treats minor cuts, scrapes and abrasion
Helps prevent infection

Store at 68°-77°F (20°-25°C)

Green Guard

2 fl oz (59.1mL)